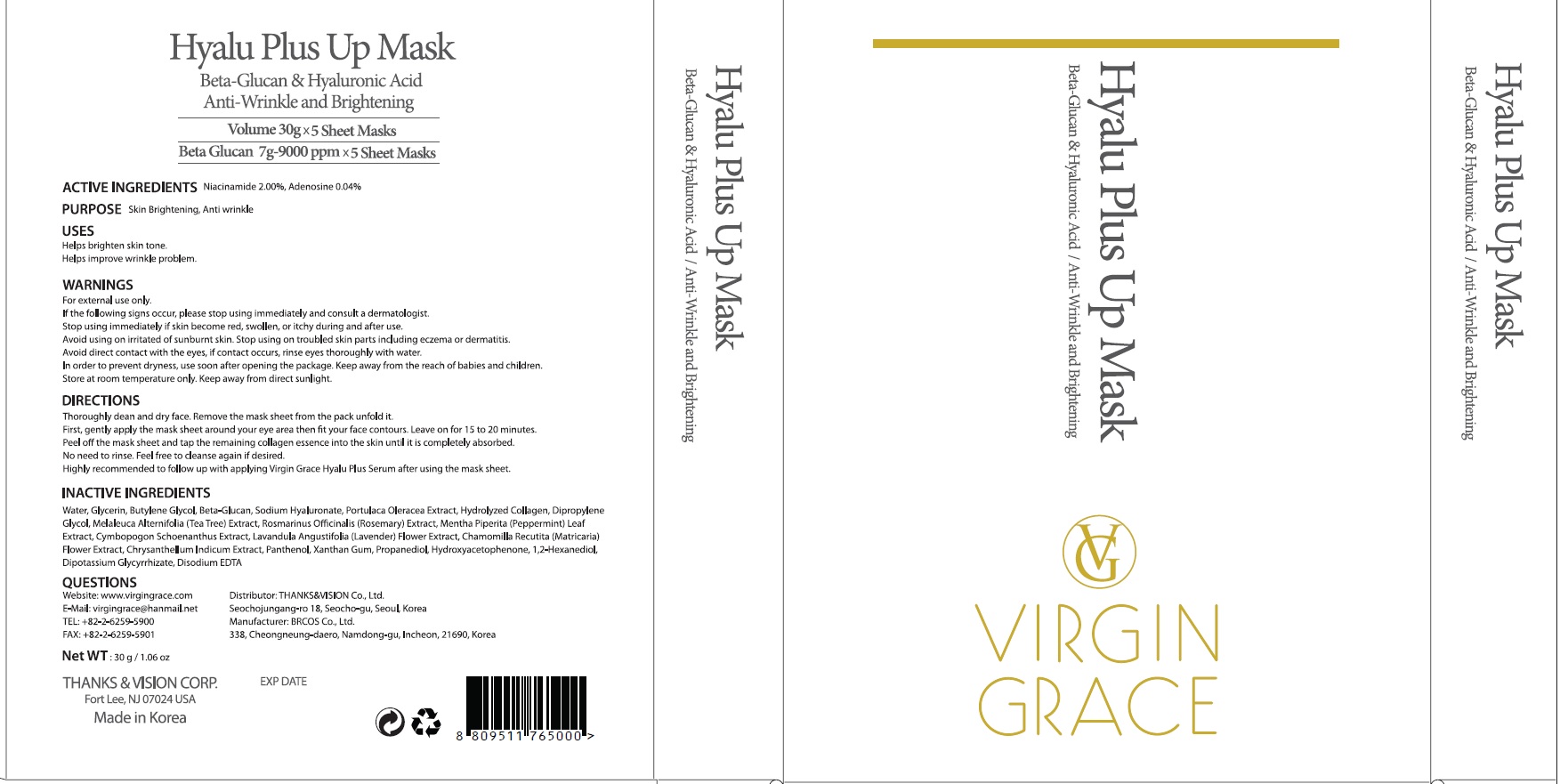 DRUG LABEL: Hyalu Plus Up Mask
NDC: 73340-010 | Form: PATCH
Manufacturer: Thanks & Vision Co., Ltd.
Category: otc | Type: HUMAN OTC DRUG LABEL
Date: 20190917

ACTIVE INGREDIENTS: Niacinamide 0.60 g/30 g; Adenosine 0.01 g/30 g
INACTIVE INGREDIENTS: Water; Glycerin

ACTIVE INGREDIENT

Active Ingredient: Niacinamide 2.00%, Adenosine 0.04%

INACTIVE INGREDIENT

Inactive Ingredients:

Water, Glycerin, Butylene Glycol, Beta-Glucan, Sodium Hyaluronate, Portulaca Oleracea Extract, Hydrolyzed Collagen, Dipropylene Glycol, Melaleuca Alternifolia (Tea Tree) Extract, Rosmarinus Officinalis (Rosemary) Extract, Mentha Piperita (Peppermint) Leaf Extract, Cymbopogon Schoenanthus Extract, Lavandula Angustifolia (Lavender) Flower Extract, Chamomilla Recutita (Matricaria) Flower Extract, Chrysanthellum Indicum Extract, Panthenol, Xanthan Gum, Propanediol, Hydroxyacetophenone, 1,2-Hexanediol, Dipotassium Glycyrrhizate, Disodium EDTA

PURPOSE

Purpose: Skin Brightening, Anti wrinkle

WARNINGS

For external use only.
If the following signs occur, please stop using immediately and consult a dermatologist.
Stop using immediately if skin become red, swollen, or itchy during and after use.
Avoid using on irritated of sunburnt skin. Stop using on troubled skin parts including eczema or dermatitis.
Avoid direct contact with the eyes, if contact occurs, rinse eyes thoroughly with water.
In order to prevent dryness, use soon after opening the package. Keep away from the reach of babies and children.
Store at room temperature only. Keep away from direct sunlight.

KEEP OUT OF REACH OF CHILDREN

Keep away from the reach of babies and children.

Uses

Helps brighten skin tone.
Helps improve wrinkle problem.

Directions

Thoroughly dean and dry face. Remove the mask sheet from the pack unfold it.
First, gently apply the mask sheet around your eye area then fit your face contours. Leave on for 15 to 20 minutes.
Peel off the mask sheet and tap the remaining collagen essence into the skin until it is completely absorbed.
No need to rinse. Feel free to cleanse again if desired.
Highly recommended to follow up with applying Virgin Grace Hyalu Plus Serum after using the mask sheet.